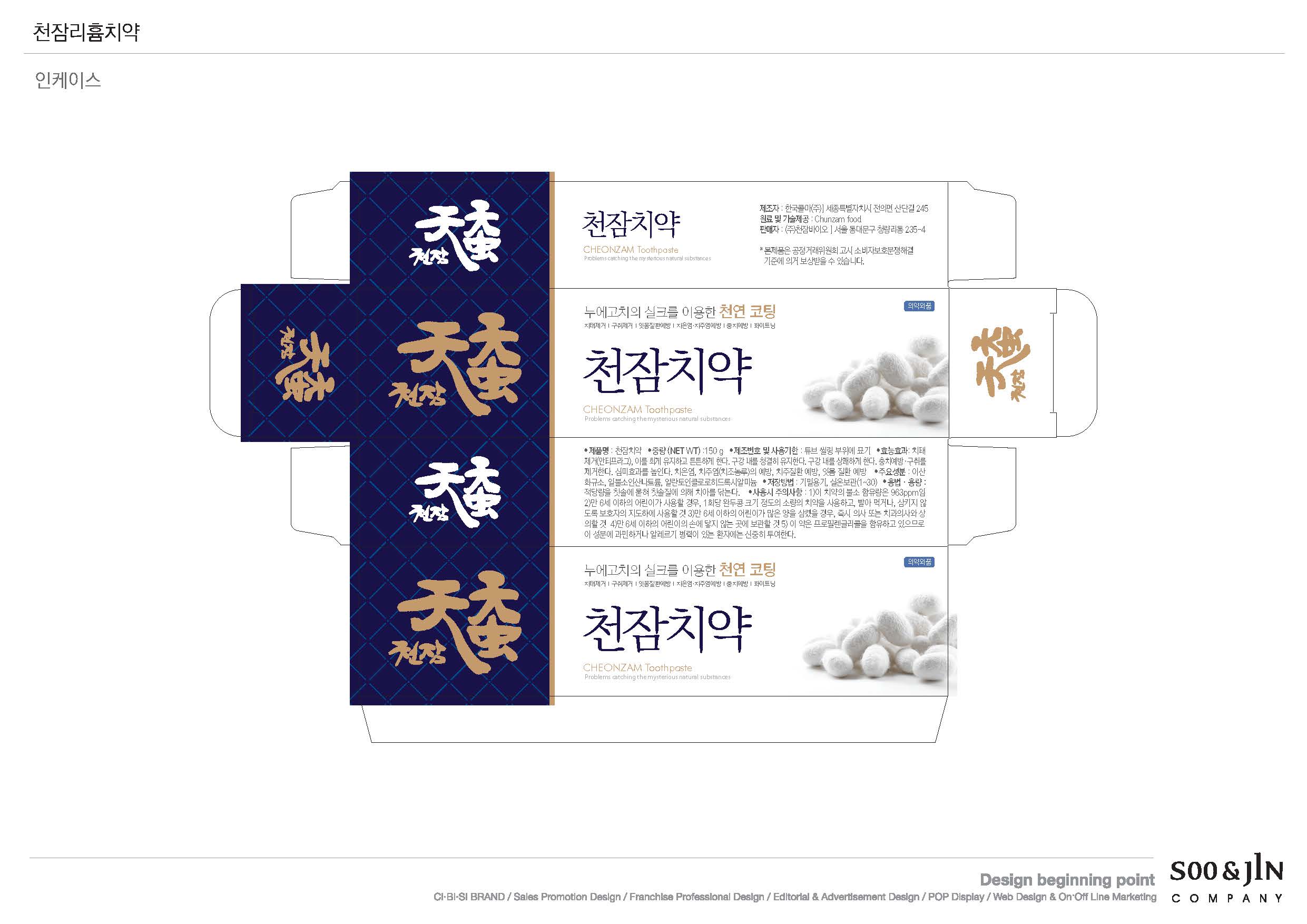 DRUG LABEL: Chunzam Silk Amino Acid Tooth
NDC: 71078-0001 | Form: PASTE, DENTIFRICE
Manufacturer: CHUNZAM BIO CO LTD
Category: otc | Type: HUMAN OTC DRUG LABEL
Date: 20171026

ACTIVE INGREDIENTS: .ALPHA.-TOCOPHEROL ACETATE 0.1 g/100 g; SILICON DIOXIDE 4 g/100 g; SODIUM MONOFLUOROPHOSPHATE 0.33 g/100 g
INACTIVE INGREDIENTS: PROPOLIS WAX

ACTIVE INGREDIENT

Silicon Dioxide, Sodium Monofluorophosphate, Tocopherol acetate

INACTIVE INGREDIENT

D-Sorbitol, Propolis Extract, ETC

PURPOSE

For dental care

Keep out of reach of children

INDICATIONS AND USAGE

apply proper amount on your toothbrush, brush teeth

WARNINGS

- do not swallow when using this product
- if more than used for rinsing is accidentally swallowed, get medical helps or contact a poison control center right away

DOSAGE AND ADMINISTRATION

use when is needed